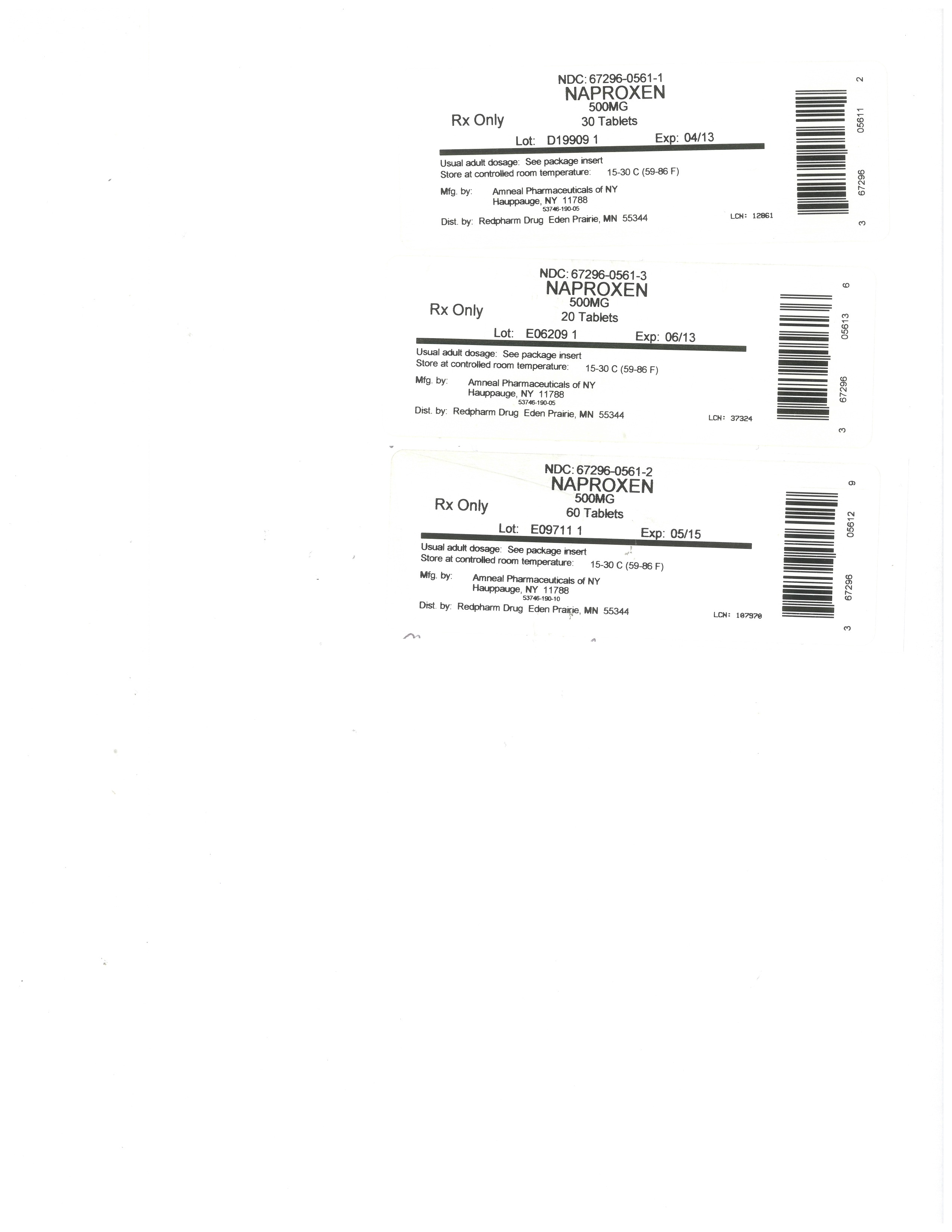 DRUG LABEL: Naproxen
NDC: 67296-0561 | Form: TABLET
Manufacturer: RedPharm Drug, Inc.
Category: prescription | Type: HUMAN PRESCRIPTION DRUG LABEL
Date: 20220119

ACTIVE INGREDIENTS: NAPROXEN 500 mg/1 1
INACTIVE INGREDIENTS: CROSCARMELLOSE SODIUM; POVIDONE; MAGNESIUM STEARATE

BOXED WARNING

Cardiovascular Risk

NSAIDs may cause an increased risk of serious cardiovascular thrombotic events, myocardial infarction, and stroke, which can be fatal. This risk may increase with duration of use. Patients with cardiovascular disease or risk factors for cardiovascular disease may be at greater risk (see WARNINGS).
Naproxen as Naproxen Tablets, USP is contraindicated for the treatment of peri-operative pain in the setting of coronary artery bypass graft (CABG) surgery (see WARNINGS).

Gastrointestinal Risk

NSAIDs cause an increased risk of serious gastrointestinal adverse events including bleeding, ulceration, and perforation of the stomach or intestines, which can be fatal. These events can occur at any time during use and without warning symptoms. Elderly patients are at greater risk for serious gastrointestinal events (see WARNINGS).

DESCRIPTION

Naproxen, USP is a propionic acid derivative related to the arylacetic acid group of nonsteroidal anti-inflammatory drugs.

The chemical name for naproxen, USP is (S)-6-methoxy-α-methyl-2-naphthaleneacetic acid. Naproxen, USP has the following structure:

[Formula Structure]

Naproxen, USP has a molecular weight of 230.26 and a molecular formula of C14H14O3.

Naproxen, USP is an odorless, white to off-white crystalline substance. It is lipid-soluble, practically insoluble in water at low pH and freely soluble in water at high pH. The octanol/water partition coefficient of naproxen, USP at pH 7.4 is 1.6 to 1.8.

Naproxen, USP is available as white tablets containing 250 mg of naproxen, USP, white tablets containing 375 mg of naproxen, USP and white tablets containing 500 mg of naproxen, USP for oral administration. The inactive ingredients are croscarmellose sodium, povidone and magnesium stearate.

CLINICAL PHARMACOLOGY

Pharmacodynamics

Naproxen is a nonsteroidal anti-inflammatory drug (NSAID) with analgesic and antipyretic properties. The mechanism of action of the naproxen anion, like that of other NSAIDs, is not completely understood but may be related to prostaglandin synthetase inhibition.

Pharmacokinetics

Naproxen is rapidly and completely absorbed from the gastrointestinal tract with an in vivobioavailability of 95%. The different dosage forms of naproxen are bioequivalent in terms of extent of absorption (AUC) and peak concentration (Cmax); however, the products do differ in their pattern of absorption. These differences between naproxen products are related to both the chemical form of naproxen used and its formulation. Even with the observed differences in pattern of absorption, the elimination half-life of naproxen is unchanged across products ranging from 12 to 17 hours. Steady-state levels of naproxen are reached in 4 to 5 days, and the degree of naproxen accumulation is consistent with this half-life. This suggests that the differences in pattern of release play only a negligible role in the attainment of steady-state plasma levels.

Absorption

Immediate Release
After administration of Naproxen Tablets, peak plasma levels are attained in 2 to 4 hours.

Distribution

Naproxen has a volume of distribution of 0.16 L/kg. At therapeutic levels naproxen is greater than 99% albumin-bound. At doses of naproxen greater than 500 mg/day there is less than proportional increase in plasma levels due to an increase in clearance caused by saturation of plasma protein binding at higher doses (average trough Css 36.5, 49.2, and 56.4 mg/L with 500, 1000 and 1500 mg daily doses of naproxen, respectively). The naproxen anion has been found in milk of lactating women at a concentration equivalent to approximately 1% of maximum naproxen concentration in plasma (see PRECAUTIONS: NURSING MOTHERS).

Metabolism

Naproxen is extensively metabolized in the liver to 6-0-desmethyl naproxen, and both parent and metabolites do not induce metabolizing enzymes. Both naproxen and 6-0-desmethyl naproxen are further metabolized to their respective acylglucuronide conjugated metabolites.

Excretion

The clearance of naproxen is 0.13 mL/min/kg. Approximately 95% of the naproxen from any dose is excreted in the urine, primarily as naproxen (<1%), 6-0-desmethyl naproxen (<1%) or their conjugates (66% to 92%). The plasma half-life of the naproxen anion in humans ranges from 12 to 17 hours. The corresponding half-lives of both naproxen’s metabolites and conjugates are shorter than 12 hours, and their rates of excretion have been found to coincide closely with the rate of naproxen disappearance from the plasma.

Small amounts, 3% or less of the administered dose, are excreted in the feces. In patients with renal failure metabolites may accumulate (see WARNINGS: RENAL EFFECTS).

Special Populations

Geriatric Patients
Studies indicate that although total plasma concentration of naproxen is unchanged, the unbound plasma fraction of naproxen is increased in the elderly, although the unbound fraction is < 1% of the total naproxen concentration. Unbound trough naproxen concentrations in elderly subjects have been reported to range from 0.12% to 0.19% of total naproxen concentration, compared with 0.05% to 0.075% in younger subjects. The clinical significance of this finding is unclear, although it is possible that the increase in free naproxen concentration could be associated with an increase in the rate of adverse events per a given dosage in some elderly patients.

Race
Pharmacokinetic differences due to race have not been studied.

Hepatic Insufficiency
Naproxen pharmacokinetics has not been determined in subjects with hepatic insufficiency.

Renal Insufficiency
Naproxen pharmacokinetics has not been determined in subjects with renal insufficiency. Given that naproxen, its metabolites and conjugates are primarily excreted by the kidney, the potential exists for naproxen metabolites to accumulate in the presence of renal insufficiency. Elimination of naproxen is decreased in patients with severe renal impairment. Naproxen-containing products are not recommended for use in patients with moderate to severe and severe renal impairment (creatinine clearance <30 mL/min) (see WARNINGS: RENAL EFFECTS).

CLINICAL STUDIES

General Information

Naproxen has been studied in patients with rheumatoid arthritis, osteoarthritis, juvenile arthritis, ankylosing spondylitis, tendonitis and bursitis, and acute gout. Improvement in patients treated for rheumatoid arthritis was demonstrated by a reduction in joint swelling, a reduction in duration of morning stiffness, a reduction in disease activity as assessed by both the investigator and patient, and by increased mobility as demonstrated by a reduction in walking time. Generally, response to naproxen has not been found to be dependent on age, sex, severity or duration of rheumatoid arthritis.

In patients with osteoarthritis, the therapeutic action of naproxen has been shown by a reduction in joint pain or tenderness, an increase in range of motion in knee joints, increased mobility as demonstrated by a reduction in walking time, and improvement in capacity to perform activities of daily living impaired by the disease.

In a clinical trial comparing standard formulations of naproxen 375 mg bid (750 mg/day) vs 750 mg bid (1500 mg/day), 9 patients in the 750 mg group terminated prematurely because of adverse events. Nineteen patients in the 1500 mg group terminated prematurely because of adverse events. Most of these adverse events were gastrointestinal events.

In clinical studies in patients with rheumatoid arthritis, osteoarthritis, and juvenile arthritis, naproxen has been shown to be comparable to aspirin and indomethacin in controlling the aforementioned measures of disease activity, but the frequency and severity of the milder gastrointestinal adverse effects (nausea, dyspepsia, heartburn) and nervous system adverse effects (tinnitus, dizziness, lightheadedness) were less in naproxen-treated patients than in those treated with aspirin or indomethacin.

In patients with ankylosing spondylitis, naproxen has been shown to decrease night pain, morning stiffness and pain at rest. In double-blind studies the drug was shown to be as effective as aspirin, but with fewer side effects.

In patients with acute gout, a favorable response to naproxen was shown by significant clearing of inflammatory changes (e.g., decrease in swelling, heat) within 24 to 48 hours, as well as by relief of pain and tenderness.

Naproxen has been studied in patients with mild to moderate pain secondary to postoperative, orthopedic, postpartum episiotomy and uterine contraction pain and dysmenorrhea. Onset of pain relief can begin within 1 hour in patients taking naproxen. Analgesic effect was shown by such measures as reduction of pain intensity scores, increase in pain relief scores, decrease in numbers of patients requiring additional analgesic medication, and delay in time to remedication. The analgesic effect has been found to last for up to 12 hours.

Naproxen may be used safely in combination with gold salts and/or corticosteroids; however, in controlled clinical trials, when added to the regimen of patients receiving corticosteroids, it did not appear to cause greater improvement over that seen with corticosteroids alone. Whether naproxen has a “steroid-sparing” effect has not been adequately studied. When added to the regimen of patients receiving gold salts, naproxen did result in greater improvement. Its use in combination with salicylates is not recommended because there is evidence that aspirin increases the rate of excretion of naproxen and data are inadequate to demonstrate that naproxen and aspirin produce greater improvement over that achieved with aspirin alone. In addition, as with other NSAIDS, the combination may result in higher frequency of adverse events than demonstrated for either product alone.

In 51Cr blood loss and gastroscopy studies with normal volunteers, daily administration of 1000 mg of naproxen as 1000 mg of naproxen tablets has been demonstrated to cause statistically significantly less gastric bleeding and erosion than 3250 mg of aspirin.

Geriatric Patients

The hepatic and renal tolerability of long-term naproxen administration was studied in two double-blind clinical trials involving 586 patients. Of the patients studied, 98 patients were age 65 and older and 10 of the 98 patients were age 75 and older. Naproxen was administered at doses of 375 mg twice daily or 750 mg twice daily for up to 6 months. Transient abnormalities of laboratory tests assessing hepatic and renal function were noted in some patients, although there were no differences noted in the occurrence of abnormal values among different age groups.

INDICATIONS AND USAGE

Carefully consider the potential benefits and risks of naproxen tablets, USP and other treatment options before deciding to use naproxen tablets, USP. Use the lowest effective dose for the shortest duration consistent with individual patient treatment goals (see WARNINGS).

Naproxen, USP as naproxen tablets, USP is indicated:

For the relief of the signs and symptoms of rheumatoid arthritis
For the relief of the signs and symptoms of osteoarthritis
For the relief of the signs and symptoms of ankylosing spondylitis
For the relief of the signs and symptoms of juvenile arthritis
For relief of the signs and symptoms of tendonitis
For relief of the signs and symptoms of bursitis
For relief of the signs and symptoms of acute gout
For the management of pain
For the management of primary dysmenorrhea

CONTRAINDICATIONS

Naproxen tablets, USP are contraindicated in patients with known hypersensitivity to naproxen, USP.

Naproxen tablets, USP should not be given to patients who have experienced asthma, urticaria, or allergic-type reactions after taking aspirin or other NSAIDs. Severe, rarely fatal, anaphylactic-like reactions to NSAIDs have been reported in such patients (see WARNINGS: ANAPHYLACTOID REACTIONS and PRECAUTIONS: PREEXISTING ASTHMA).

Naproxen tablets, USP are contraindicated for the treatment of peri-operative pain in the setting of coronary artery bypass graft (CABG) surgery (see WARNINGS).

WARNINGS

Cardiovascular Effects

Cardiovascular Thrombotic Events

Clinical trials of several COX-2 selective and nonselective NSAIDs of up to three years duration have shown an increased risk of serious cardiovascular (CV) thrombotic events, myocardial infarction, and stroke, which can be fatal. All NSAIDs, both COX-2 selective and nonselective, may have a similar risk. Patients with known CV disease or risk factors for CV disease may be at greater risk. To minimize the potential risk for an adverse CV event in patients treated with an NSAID, the lowest effective dose should be used for the shortest duration possible. Physicians and patients should remain alert for the development of such events, even in the absence of previous CV symptoms. Patients should be informed about the signs and/or symptoms of serious CV events and the steps to take if they occur.

There is no consistent evidence that concurrent use of aspirin mitigates the increased risk of serious CV thrombotic events associated with NSAID use. The concurrent use of aspirin and an NSAID does increase the risk of serious GI events (see WARNINGS: GASTROINTESTINAL EFFECTS - RISK OF ULCERATION, BLEEDING, AND PERFORATION).

Two large, controlled, clinical trials of a COX-2 selective NSAID for the treatment of pain in the first 10 to 14 days following CABG surgery found an increased incidence of myocardial infarction and stroke (see CONTRAINDICATIONS).

Hypertension

NSAIDs, including naproxen tablets, can lead to onset of new hypertension or worsening of preexisting hypertension, either of which may contribute to the increased incidence of CV events. Patients taking thiazides or loop diuretics may have impaired response to these therapies when taking NSAIDs. NSAIDs, including naproxen tablets, should be used with caution in patients with hypertension. Blood pressure (BP) should be monitored closely during the initiation of NSAID treatment and throughout the course of therapy.

Congestive Heart Failure and Edema

Fluid retention, edema, and peripheral edema have been observed in some patients taking NSAIDs. Naproxen tablets should be used with caution in patients with fluid retention, hypertension, or heart failure.

Gastrointestinal Effects- Risk of Ulceration, Bleeding, and Perforation

NSAIDs, including naproxen tablets, can cause serious gastrointestinal (GI) adverse events including inflammation, bleeding, ulceration, and perforation of the stomach, small intestine, or large intestine, which can be fatal.

These serious adverse events can occur at any time, with or without warning symptoms, in patients treated with NSAIDs. Only one in five patients, who develop a serious upper GI adverse event on NSAID therapy, is symptomatic. Upper GI ulcers, gross bleeding, or perforation caused by NSAIDs occur in approximately 1% of patients treated for 3 to 6 months, and in about 2% to 4% of patients treated for one year. These trends continue with longer duration of use, increasing the likelihood of developing a serious GI event at some time during the course of therapy. However, even short-term therapy is not without risk. The utility of periodic laboratory monitoring has not been demonstrated, nor has it been adequately assessed. Only 1 in 5 patients who develop a serious GI adverse event on NSAID therapy is symptomatic.

NSAIDs should be prescribed with extreme caution in those with a prior history of ulcer disease or gastrointestinal bleeding. Patients with a prior history of peptic ulcer disease and/or gastrointestinal bleeding who use NSAIDs have a greater than 10-fold increased risk for developing a GI bleed compared to patients with neither of these risk factors.

Other factors that increase the risk for GI bleeding in patients treated with NSAIDs include concomitant use of oral corticosteroids or anticoagulants, longer duration of NSAID therapy, smoking, use of alcohol, older age, and poor general health status. Most spontaneous reports of fatal GI events are in elderly or debilitated patients and therefore, special care should be taken in treating this population. To minimize the potential risk for an adverse GI event in patients treated with an NSAID, the lowest effective dose should be used for the shortest possible duration. Patients and physicians should remain alert for signs and symptoms of GI ulceration and bleeding during NSAID therapy and promptly initiate additional evaluation and treatment if a serious GI adverse event is suspected. This should include discontinuation of the NSAID until a serious GI adverse event is ruled out. For high risk patients, alternate therapies that do not involve NSAIDs should be considered.

Epidemiological studies, both of the case-control and cohort design, have demonstrated an association between use of psychotropic drugs that interfere with serotonin reuptake and the occurrence of upper gastrointestinal bleeding. In two studies, concurrent use of an NSAID or aspirin potentiated the risk of bleeding (see PRECAUTIONS: DRUG INTERACTIONS). Although these studies focused on upper gastrointestinal bleeding, there is no reason to believe that bleeding at other sites may be similarly potentiated.

NSAIDs should be given with care to patients with a history of inflammatory bowel disease (ulcerative colitis, Crohn’s disease) as their condition may be exacerbated.

Renal Effects

Long-term administration of NSAIDs has resulted in renal papillary necrosis and other renal injury. Renal toxicity has also been seen in patients in whom renal prostaglandins have a compensatory role in the maintenance of renal perfusion. In these patients, administration of a nonsteroidal anti-inflammatory drug may cause a dose-dependent reduction in prostaglandin formation and, secondarily, in renal blood flow, which may precipitate overt renal decompensation. Patients at greatest risk of this reaction are those with impaired renal function, hypovolemia, heart failure, liver dysfunction, salt depletion, those taking diuretics and angiotensin converting enzyme (ACE) inhibitors or angiotensin receptor blockers (ARBs), and the elderly. Discontinuation of nonsteroidal anti-inflammatory drug therapy is usually followed by recovery to the pretreatment state (see WARNINGS: ADVANCED RENAL DISEASE).

Advanced Renal Disease

No information is available from controlled clinical studies regarding the use of naproxen tablets in patients with advanced renal disease. Therefore, treatment with naproxen tablets is not recommended in these patients with advanced renal disease. If naproxen tablets therapy must be initiated, close monitoring of the patient’s renal function is advisable and patients should be adequately hydrated.

Anaphylactoid Reactions

As with other NSAIDs, anaphylactoid reactions may occur in patients without known prior exposure to naproxen tablets. Naproxen tablets should not be given to patients with the aspirin triad. This symptom complex typically occurs in asthmatic patients who experience rhinitis with or without nasal polyps, or who exhibit severe, potentially fatal bronchospasm after taking aspirin or other NSAIDs (see CONTRAINDICATIONS and PRECAUTIONS: PREEXISTING ASTHMA). Emergency help should be sought in cases where an anaphylactoid reaction occurs. Anaphylactoid reactions, like anaphylaxis, may have a fatal outcome.

Skin Reactions

NSAIDs, including naproxen tablets, can cause serious skin adverse events such as exfoliative dermatitis, Stevens-Johnson Syndrome (SJS), and toxic epidermal necrolysis (TEN), which can be fatal. These serious events may occur without warning. Patients should be informed about the signs and symptoms of serious skin manifestations and use of the drug should be discontinued at the first appearance of skin rash or any other sign of hypersensitivity.

Pregnancy

In late pregnancy, as with other NSAIDs, naproxen tablets should be avoided because it may cause premature closure of the ductus arteriosus.

PRECAUTIONS

General

Naproxen-containing products such as naproxen tablets, and other naproxen products should not be used concomitantly since they all circulate in the plasma as the naproxen anion.

Naproxen tablets cannot be expected to substitute for corticosteroids or to treat corticosteroid insufficiency. Abrupt discontinuation of corticosteroids may lead to disease exacerbation. Patients on prolonged corticosteroid therapy should have their therapy tapered slowly if a decision is made to discontinue corticosteroids and the patient should be observed closely for any evidence of adverse effects, including adrenal insufficiency and exacerbation of symptoms of arthritis.

Patients with initial hemoglobin values of 10 g or less who are to receive a long-term therapy should have hemoglobin values determined periodically.

The pharmacological activity of naproxen tablets in reducing fever and inflammation may diminish the utility of these diagnostic signs in detecting complications of presumed noninfectious, noninflammatory painful conditions.

Because of adverse eye findings in animal studies with drugs of this class, it is recommended that ophthalmic studies be carried out if any change or disturbance in vision occurs.

Hepatic Effects

Borderline elevations of one or more liver tests may occur in up to 15% of patients taking NSAIDs including naproxen tablets. Hepatic abnormalities may be the result of hypersensitivity rather than direct toxicity. These laboratory abnormalities may progress, may remain essentially unchanged, or may be transient with continuing therapy. The SGPT (ALT) test is probably the most sensitive indicator of liver dysfunction. Notable elevations of ALT or AST (approximately three or more times the upper limit of normal) have been reported in approximately 1% of patients in clinical trials with NSAIDs. In addition, rare cases of severe hepatic reactions, including jaundice and fatal fulminant hepatitis, liver necrosis and hepatic failure, some of them with fatal outcomes have been reported.

A patient with symptoms and/or signs suggesting liver dysfunction, or in whom an abnormal liver test has occurred, should be evaluated for evidence of the development of more severe hepatic reaction while on therapy with naproxen tablets.

If clinical signs and symptoms consistent with liver disease develop, or if systemic manifestations occur (e.g., eosinophilia, rash, etc.), naproxen tablets should be discontinued.

Chronic alcoholic liver disease and probably other diseases with decreased or abnormal plasma proteins (albumin) reduce the total plasma concentration of naproxen, but the plasma concentration of unbound naproxen is increased. Caution is advised when high doses are required and some adjustment of dosage may be required in these patients. It is prudent to use the lowest effective dose.

Hematological Effects

Anemia is sometimes seen in patients receiving NSAIDs, including naproxen tablets. This may be due to fluid retention, occult or gross GI blood loss, or an incompletely described effect upon erythropoiesis. Patients on long-term treatment with NSAIDs, including naproxen tablets, should have their hemoglobin or hematocrit checked if they exhibit any signs or symptoms of anemia.

NSAIDs inhibit platelet aggregation and have been shown to prolong bleeding time in some patients. Unlike aspirin, their effect on platelet function is quantitatively less, of shorter duration, and reversible. Patients receiving naproxen tablets who may be adversely affected by alterations in platelet function, such as those with coagulation disorders or patients receiving anticoagulants, should be carefully monitored.

Preexisting Asthma

Patients with asthma may have aspirin-sensitive asthma. The use of aspirin in patients with aspirin-sensitive asthma has been associated with severe bronchospasm, which can be fatal. Since cross reactivity, including bronchospasm, between aspirin and other nonsteroidal anti-inflammatory drugs has been reported in such aspirin-sensitive patients, naproxen tablets should not be administered to patients with this form of aspirin sensitivity and should be used with caution in patients with preexisting asthma.

Information for Patients

Patients should be informed of the following information before initiating therapy with an NSAID and periodically during the course of ongoing therapy. Patients should also be encouraged to read the NSAID Medication Guide that accompanies each prescription dispensed.

Naproxen tablets, like other NSAIDs, may cause serious CV side effects, such as MI or stroke, which may result in hospitalization and even death. Although serious CV events can occur without warning symptoms, patients should be alert for the signs and symptoms of chest pain, shortness of breath, weakness, slurring of speech, and should ask for medical advice when observing any indicative sign or symptoms. Patients should be apprised of the importance of this follow-up (see WARNINGS: CARDIOVASCULAR EFFECTS).
Naproxen tablets, like other NSAIDs, can cause GI discomfort and, rarely, serious GI side effects, such as ulcers and bleeding, which may result in hospitalization and even death. Although serious GI tract ulcerations and bleeding can occur without warning symptoms, patients should be alert for the signs and symptoms of ulcerations and bleeding, and should ask for medical advice when observing any indicative signs or symptoms including epigastric pain, dyspepsia, melena, and hematemesis. Patients should be apprised of the importance of this follow-up (see WARNINGS: GASTROINTESTINAL EFFECTS- RISK OF ULCERATION, BLEEDING, AND
PERFORATION).
Naproxen tablets, like other NSAIDs, can cause serious skin side effects such as exfoliative dermatitis, SJS, and TEN, which may result in hospitalizations and even death. Although serious skin reactions may occur without warning, patients should be alert for the signs and symptoms of skin rash and blisters, fever, or other signs of hypersensitivity such as itching, and should ask for medical advice when observing any indicative signs or symptoms. Patients should be advised to stop the drug immediately if they develop any type of rash and contact their physicians as soon as possible.
Patients should promptly report signs or symptoms of unexplained weight gain or edema to their physicians.
Patients should be informed of the warning signs and symptoms of hepatotoxicity (e.g., nausea, fatigue, lethargy, pruritus, jaundice, right upper quadrant tenderness, and “flu-like” symptoms). If these occur, patients should be instructed to stop therapy and seek immediate medical therapy.
Patients should be informed of the signs of an anaphylactoid reaction (e.g., difficulty breathing, swelling of the face or throat). If these occur, patients should be instructed to seek immediate emergency help (see WARNINGS).
In late pregnancy, as with other NSAIDs, naproxen tablets should be avoided because it may cause premature closure of the ductus arteriosus.
Caution should be exercised by patients whose activities require alertness if they experience drowsiness, dizziness, vertigo or depression during therapy with naproxen.

Laboratory Tests

Because serious GI tract ulcerations and bleeding can occur without warning symptoms, physicians should monitor for signs or symptoms of GI bleeding. Patients on long-term treatment with NSAIDs should have their CBC and a chemistry profile checked periodically. If clinical signs and symptoms consistent with liver or renal disease develop, systemic manifestations occur (e.g., eosinophilia, rash, etc.) or if abnormal liver tests persist or worsen, naproxen tablets should be discontinued.

Drug Interactions

Angiotensin Converting Enzyme (ACE)-inhibitors/Angiotensin Receptor Blockers (ARBs)

NSAIDs may diminish the antihypertensive effect of ACE-inhibitors, ARBs, or beta-blockers (including propranolol).

Monitor patients taking NSAIDs concomitantly with ACE-inhibitors, ARBs, or beta-blockers for changes in blood pressure.

In addition, in patients who are elderly, volume-depleted (including those on diuretic therapy), or have compromised renal function, co-administration of NSAIDs with ACE inhibitors or ARBs may result in deterioration of renal function, including possible acute renal failure. Monitor these patients closely for signs of worsening renal function.

Antacids and Sucralfate

Concomitant administration of some antacids (magnesium oxide or aluminum hydroxide) and sucralfate can delay the absorption of naproxen.

Aspirin

When naproxen as naproxen tablets is administered with aspirin, its protein binding is reduced, although the clearance of free naproxen tablets is not altered. The clinical significance of this interaction is not known; however, as with other NSAIDs, concomitant administration of naproxen and aspirin is not generally recommended because of the potential of increased adverse effects.

Cholestyramine

As with other NSAIDs, concomitant administration of cholestyramine can delay the absorption of naproxen.

Diuretics

Clinical studies, as well as postmarketing observations, have shown that naproxen tablets can reduce the natriuretic effect of furosemide and thiazides in some patients. This response has been attributed to inhibition of renal prostaglandin synthesis. During concomitant therapy with NSAIDs, the patient should be observed closely for signs of renal failure (see WARNINGS: RENAL EFFECTS), as well as to assure diuretic efficacy.

Lithium

NSAIDs have produced an elevation of plasma lithium levels and a reduction in renal lithium clearance. The mean minimum lithium concentration increased 15% and the renal clearance was decreased by approximately 20%. These effects have been attributed to inhibition of renal prostaglandin synthesis by the NSAID. Thus, when NSAIDs and lithium are administered concurrently, subjects should be observed carefully for signs of lithium toxicity.

Methotrexate

NSAIDs have been reported to competitively inhibit methotrexate accumulation in rabbit kidney slices. Naproxen and other nonsteroidal anti-inflammatory drugs have been reported to reduce the tubular secretion of methotrexate in an animal model. This may indicate that they could enhance the toxicity of methotrexate. Caution should be used when NSAIDs are administered concomitantly with methotrexate.

Warfarin

The effects of warfarin and NSAIDs on GI bleeding are synergistic, such that users of both drugs together have a risk of serious GI bleeding higher than users of either drug alone. No significant interactions have been observed in clinical studies with naproxen and coumarin-type anticoagulants. However, caution is advised since interactions have been seen with other nonsteroidal agents of this class. The free fraction of warfarin may increase substantially in some subjects and naproxen interferes with platelet function.

Selective Serotonin Reuptake Inhibitors (SSRIs)

There is an increased risk of gastrointestinal bleeding when selective serotonin reuptake inhibitors (SSRIs) are combined with NSAIDs. Caution should be used when NSAIDs are administered concomitantly with SSRIs.

Other Information Concerning Drug Interactions

Naproxen is highly bound to plasma albumin; it thus has a theoretical potential for interaction with other albumin-bound drugs such as coumarin-type anticoagulants, sulphonylureas, hydantoins, other NSAIDs, and aspirin. Patients simultaneously receiving naproxen and a hydantoin, sulphonamide or sulphonylurea should be observed for adjustment of dose if required.

Probenecid given concurrently increases naproxen anion plasma levels and extends its plasma half-life significantly.

Drug/Laboratory Test Interactions

Naproxen may decrease platelet aggregation and prolong bleeding time. This effect should be kept in mind when bleeding times are determined.

The administration of naproxen may result in increased urinary values for 17-ketogenic steroids because of an interaction between the drug and/or its metabolites with m-di-nitrobenzene used in this assay. Although 17-hydroxy-corticosteroid measurements (Porter-Silber test) do not appear to be artifactually altered, it is suggested that therapy with naproxen be temporarily discontinued 72 hours before adrenal function tests are performed if the Porter-Silber test is to be used.

Naproxen may interfere with some urinary assays of 5-hydroxy indoleacetic acid (5HIAA).

Carcinogenesis

A 2-year study was performed in rats to evaluate the carcinogenic potential of naproxen at rat doses of 8, 16, and 24 mg/kg/day (50, 100, and 150 mg/m2). The maximum dose used was 0.28 times the systemic exposure to humans at the recommended dose. No evidence of tumorigenicity was found.

Pregnancy

Teratogenic Effects

Pregnancy Category C

Reproduction studies have been performed in rats at 20 mg/kg/day (125 mg/m2/day, 0.23 times the human systemic exposure), rabbits at 20 mg/kg/day (220 mg/m2/day, 0.27 times the human systemic exposure), and mice at 170 mg/kg/day (510 mg/m2/day, 0.28 times the human systemic exposure) with no evidence of impaired fertility or harm to the fetus due to the drug. However, animal reproduction studies are not always predictive of human response. There are no adequate and well-controlled studies in pregnant women. Naproxen tablets should be used in pregnancy only if the potential benefit justifies the potential risk to the fetus.

Nonteratogenic Effects

There is some evidence to suggest that when inhibitors of prostaglandin synthesis are used to delay preterm labor there is an increased risk of neonatal complications such as necrotizing enterocolitis, patent ductus arteriosus and intracranial hemorrhage. Naproxen treatment given in late pregnancy to delay parturition has been associated with persistent pulmonary hypertension, renal dysfunction and abnormal prostaglandin E levels in preterm infants. Because of the known effects of nonsteroidal anti-inflammatory drugs on the fetal cardiovascular system (closure of ductus arteriosus), use during pregnancy (particularly late pregnancy) should be avoided.

Labor and Delivery

In rat studies with NSAIDs, as with other drugs known to inhibit prostaglandin synthesis, an increased incidence of dystocia, delayed parturition, and decreased pup survival occurred. Naproxen-containing products are not recommended in labor and delivery because, through its prostaglandin synthesis inhibitory effect, naproxen may adversely affect fetal circulation and inhibit uterine contractions, thus increasing the risk of uterine hemorrhage. The effects of naproxen tablets on labor and delivery in pregnant women are unknown.

Nursing Mothers

The naproxen anion has been found in the milk of lactating women at a concentration equivalent to approximately 1% of maximum naproxen concentration in plasma. Because of the possible adverse effects of prostaglandin-inhibiting drugs on neonates, use in nursing mothers should be avoided.

Pediatric Use

Safety and effectiveness in pediatric patients below the age of 2 years have not been established.

Geriatric Use

Studies indicate that although total plasma concentration of naproxen is unchanged, the unbound plasma fraction of naproxen is increased in the elderly. Caution is advised when high doses are required and some adjustment of dosage may be required in elderly patients. As with other drugs used in the elderly, it is prudent to use the lowest effective dose.

Experience indicates that geriatric patients may be particularly sensitive to certain adverse effects of nonsteroidal anti-inflammatory drugs. Elderly or debilitated patients seem to tolerate peptic ulceration or bleeding less well when these events do occur. Most spontaneous reports of fatal GI events are in the geriatric population (see WARNINGS).

Naproxen is known to be substantially excreted by the kidney, and the risk of toxic reactions to this drug may be greater in patients with impaired renal function. Because elderly patients are more likely to have decreased renal function, care should be taken in dose selection, and it may be useful to monitor renal function. Geriatric patients may be at a greater risk for the development of a form of renal toxicity precipitated by reduced prostaglandin formation during administration of nonsteroidal anti-inflammatory drugs (see WARNINGS: RENAL EFFECTS).

ADVERSE REACTIONS

Adverse reactions reported in controlled clinical trials in 960 patients treated for rheumatoid arthritis or osteoarthritis are listed below. In general, reactions in patients treated chronically were reported 2 to 10 times more frequently than they were in short-term studies in the 962 patients treated for mild to moderate pain or for dysmenorrhea. The most frequent complaints reported related to the gastrointestinal tract.

A clinical study found gastrointestinal reactions to be more frequent and more severe in rheumatoid arthritis patients taking daily doses of 1500 mg naproxen compared to those taking 750 mg naproxen (see CLINICAL PHARMACOLOGY).

In controlled clinical trials with about 80 pediatric patients and in well-monitored, open-label studies with about 400 pediatric patients with juvenile arthritis treated with naproxen, the incidence of rash and prolonged bleeding times were increased, the incidence of gastrointestinal and central nervous system reactions were about the same, and the incidence of other reactions were lower in pediatric patients than in adults.

In patients taking naproxen in clinical trials, the most frequently reported adverse experiences in approximately 1% to 10% of patients are:

Gastrointestinal (GI) Experiences, including: heartburn*, abdominal pain*, nausea*, constipation*, diarrhea, dyspepsia, stomatitis

Central Nervous System: headache*, dizziness*, drowsiness*, lightheadedness, vertigo

Dermatologic: pruritus (itching)*, skin eruptions*, ecchymoses*, sweating, purpura

Special Senses: tinnitus*, visual disturbances, hearing disturbances

Cardiovascular: edema*, palpitations.

General: dyspnea*, thirst

*Incidence of reported reaction between 3% and 9%. Those reactions occurring in less than 3% of the patients are unmarked.

In patients taking NSAIDs, the following adverse experiences have also been reported in approximately 1% to 10% of patients.

Gastrointestinal (GI) Experiences, including: flatulence, gross bleeding/perforation, GI ulcers (gastric/duodenal), vomiting

General: abnormal renal function, anemia, elevated liver enzymes, increased bleeding time, rashes

The following are additional adverse experiences reported in <1% of patients taking naproxen during clinical trials and through postmarketing reports. Those adverse reactions observed through postmarketing reports are italicized.

Body as a Whole: anaphylactoid reactions, angioneurotic edema, menstrual disorders, pyrexia (chills and fever)

Cardiovascular: congestive heart failure, vasculitis, hypertension, pulmonary edema

Gastrointestinal:inflammation, bleeding(sometimes fatal, particularly in the elderly), ulceration, perforation and obstruction of the upper and lower gastrointestinal tract. Esophagitis, stomatitis, hematemesis, pancreatitis, vomiting, colitis, exacerbation of inflammatory bowel disease (ulcerative colitis, Crohn’s disease).

Hepatobiliary: jaundice, abnormal liver function tests, hepatitis (some cases have been fatal)

Hemic and Lymphatic:eosinophilia, leucopenia, melena, thrombocytopenia, agranulocytosis, granulocytopenia, hemolytic anemia, aplastic anemia

Metabolic and Nutritional:hyperglycemia, hypoglycemia

Nervous System: inability to concentrate, depression, dream abnormalities, insomnia, malaise, myalgia, muscle weakness, aseptic meningitis, cognitive dysfunction, convulsions

Respiratory:eosinophilic pneumonitis, asthma

Dermatologic: alopecia, urticaria, skin rashes, toxic epidermal necrolysis, erythema multiforme, erythema nodosum, fixed drug eruption, lichen planus, pustular reaction, systemic lupus erythematosus, bullous reactions, including Stevens-Johnson syndrome, photosensitive dermatitis, photosensitivity reactions, including rare cases resembling porphyria cutanea tarda (pseudoporphyria) or epidermolysis bullosa. If skin fragility, blistering or other symptoms suggestive of pseudoporphyria occur, treatment should be discontinued and the patient monitored.

Special Senses:hearing impairment, corneal opacity, papillitis, retrobulbar optic neuritis, papilledema

Urogenital:glomerular nephritis, hematuria, hyperkalemia, interstitial nephritis, nephrotic syndrome, renal disease, renal failure, renal papillary necrosis, raised serum creatinine

Reproduction (female):infertility

In patients taking NSAIDs, the following adverse experiences have also been reported in <1% of patients.

Body as a Whole: fever infection, sepsis, anaphylactic reactions, appetite changes, death

Cardiovascular: hypertension, tachycardia, syncope, arrhythmia, hypotension, myocardial infarction

Gastrointestinal: dry mouth, esophagitis, gastric/peptic ulcers, gastritis, glossitis, eructation

Hepatobiliary: hepatitis, liver failure

Hemic and Lymphatic: rectal bleeding, lymphadenopathy, pancytopenia

Metabolic and Nutritional: weight changes

Nervous System: anxiety, asthenia, confusion, nervousness, paresthesia, somnolence, tremors, convulsions, coma, hallucinations

Respiratory: asthma, respiratory depression, pneumonia

Dermatologic: exfoliative dermatitis

Special Senses: blurred vision, conjunctivitis

Urogenital: cystitis, dysuria, oliguria/polyuria, proteinuria

OVERDOSAGE

Symptoms and Signs

Significant naproxen overdosage may be characterized by lethargy, dizziness, drowsiness, epigastric pain, abdominal discomfort, heartburn, indigestion, nausea, transient alterations in liver function, hypoprothrombinemia, renal dysfunction, metabolic acidosis, apnea, disorientation or vomiting. Gastrointestinal bleeding can occur. Hypertension, acute renal failure, respiratory depression, and coma may occur, but are rare. Anaphylactoid reactions have been reported with therapeutic ingestion of NSAIDs, and may occur following an overdose.

Treatment

Patients should be managed by symptomatic and supportive care following a NSAID overdose. There are no specific antidotes. Hemodialysis does not decrease the plasma concentration of naproxen because of the high degree of its protein binding. Emesis and/or activated charcoal (60 to 100 g in adults, 1 to 2 g/kg in children) and/or osmotic cathartic may be indicated in patients seen within 4 hours of ingestion with symptoms or following a large overdose. Forced diuresis, alkalinization of urine or hemoperfusion may not be useful due to high protein binding.

DOSAGE AND ADMINISTRATION

Carefully consider the potential benefits and risks of naproxen tablets, USP and other treatment options before deciding to use naproxen tablets, USP. Use the lowest effective dose for the shortest duration consistent with individual patient treatment goals (see WARNINGS).

After observing the response to initial therapy with naproxen tablets, USP, the dose and frequency should be adjusted to suit an individual patient’s needs.

Different dose strengths and formulations (i.e., tablets, suspension) of the drug are not necessarily bioequivalent. This difference should be taken into consideration when changing formulation.

Although naproxen tablets, USP, naproxen suspension, naproxen delayed-release tablets, and naproxen sodium tablets all circulate in the plasma as naproxen, they have pharmacokinetic differences that may affect onset of action. Onset of pain relief can begin within 1 hour in patients taking naproxen.

The recommended strategy for initiating therapy is to choose a formulation and a starting dose likely to be effective for the patient and then adjust the dosage based on observation of benefit and/or adverse events. A lower dose should be considered in patients with renal or hepatic impairment or in elderly patients (see WARNINGS and PRECAUTIONS).

Geriatric Patients

Studies indicate that although total plasma concentration of naproxen is unchanged, the unbound plasma fraction of naproxen is increased in the elderly. Caution is advised when high doses are required and some adjustment of dosage may be required in elderly patients. As with other drugs used in the elderly, it is prudent to use the lowest effective dose.

Patients With Moderate to Severe Renal Impairment

Naproxen-containing products are not recommended for use in patients with moderate to severe and severe renal impairment (creatinine clearance <30 mL/min) (see WARNINGS: RENAL EFFECTS).

Rheumatoid Arthritis, Osteoarthritis and Ankylosing Spondylitis

Naproxen Tablets, USP

250 mg
or 375 mg
or 500 mg

twice daily
twice daily
twice daily

During long-term administration, the dose of naproxen may be adjusted up or down depending on the clinical response of the patient. A lower daily dose may suffice for long-term administration. The morning and evening doses do not have to be equal in size and the administration of the drug more frequently than twice daily is not necessary.

In patients who tolerate lower doses well, the dose may be increased to naproxen 1500 mg/day for limited periods of up to 6 months when a higher level of anti-inflammatory/ analgesic activity is required. When treating such patients with naproxen 1500 mg/day, the physician should observe sufficient increased clinical benefits to offset the potential increased risk. The morning and evening doses do not have to be equal in size and administration of the drug more frequently than twice daily does not generally make a difference in response (see CLINICAL PHARMACOLOGY).

Acute Gout

The recommended starting dose is 750 mg of naproxen tablets, USP followed by 250 mg every 8 hours until the attack has subsided.

HOW SUPPLIED

Naproxen Tablets, USP, 250 mg, are supplied as white, round, biconvex tablets, debossed with “IP 188” on obverse and “250” on the reverse. They are available as follows:

Bottles of 100: NDC 53746-188-01
Bottles of 500: NDC 53746-188-05
Bottles of 1000: NDC 53746-188-10

NaproxenTablets, USP, 375 mg, are supplied as white, capsule-shaped, biconvex tablets, debossed with “IP 189” on obverse and “375” on the reverse. They are available as follows:

Bottles of 100: NDC 53746-189-01
Bottles of 500: NDC 53746-189-05
Bottles of 1000: NDC 53746-189-10

Naproxen Tablets, USP, 500 mg, are supplied as white, capsule-shaped, biconvex tablets, debossed with “IP 190” on obverse and “500” on the reverse. They are available as follows:

Bottles of 100: NDC 53746-190-01
Bottles of 500: NDC 53746-190-05
Bottles of 1000: NDC 53746-190-10

Store at 20° to 25°C (68° to 77°F); excursions permitted to 15° to 30°C (59° to 86°F) [See USP Controlled Room Temperature]. Dispense in well-closed, light-resistant containers as defined in the USP.

Rx only

Distributed by:
Amneal Pharmaceuticals
Bridgewater, NJ 08807

Rev. 10-2015-01

MEDICATION GUIDE

Medication Guide for Nonsteroidal Anti-inflammatory Drugs (NSAIDs)

What is the most important information I should know about medicines called Nonsteroidal Anti-inflammatory Drugs (NSAIDs)? NSAIDs can cause serious side effects, including:

Increased risk of a heart attack or stroke that can lead to death. This risk may happen early in treatment and may increase:

with increasing doses of NSAIDs
with longer use of NSAIDs

Do not take NSAIDs right before or after a heart surgery called a “coronary artery bypass graft (CABG)."

Avoid taking NSAIDs after a recent heart attack, unless your healthcare provider tells you to. You may have an increased risk of another heart attack if you take NSAIDs after a recent heart attack.

Increased risk of bleeding, ulcers, and tears (perforation) of the esophagus (tube leading from the mouth to the stomach), stomach and intestines:

anytime during use
without warning symptoms
that may cause death

The risk of getting an ulcer or bleeding increases with:

past history of stomach ulcers, or stomach or intestinal bleeding with use of NSAIDs
taking medicines called “corticosteroids”, “anticoagulants”, “SSRIs”, or “SNRIs”
increasing doses of NSAIDs
longer use of NSAIDs
smoking
drinking alcohol
older age
poor health
advanced liver disease
bleeding problems

NSAIDs should only be used:

exactly as prescribed
at the lowest dose possible for your treatment
for the shortest time needed

What are NSAIDs?

NSAIDs are used to treat pain and redness, swelling, and heat (inflammation) from medical conditions such as different types of arthritis, menstrual cramps, and other types of short-term pain.

Who should not take NSAIDs? Do not take NSAIDs:

if you have had an asthma attack, hives, or other allergic reaction with aspirin or any other NSAIDs.
right before or after heart bypass surgery.

Before taking NSAIDS, tell your healthcare provider about all of your medical conditions, including if you:

have liver or kidney problems
have high blood pressure
have asthma
are pregnant or plan to become pregnant. Talk to your healthcare provider if you are considering taking NSAIDs during pregnancy. You should not take NSAIDs after 29 weeks of pregnancy.
are breastfeeding or plan to breast feed.

Tell your healthcare provider about all of the medicines you take, including prescription or over-the-counter medicines, vitamins or herbal supplements. NSAIDs and some other medicines can interact with each other and cause serious side effects. Do not start taking any new medicine without talking to your healthcare provider first.

What are the possible side effects of NSAIDs? NSAIDs can cause serious side effects, including: See “What is the most important information I should know about medicines called Nonsteroidal Anti-inflammatory Drugs (NSAIDs)?”

new or worse high blood pressure
heart failure
liver problems including liver failure
kidney problems including kidney failure
low red blood cells (anemia)
life-threatening skin reactions
life-threatening allergic reactions

Other side effects of NSAIDs include: stomach pain, constipation, diarrhea, gas, heartburn, nausea, vomiting, and dizziness. Get emergency help right away if you get any of the following symptoms:

shortness of breath or trouble breathing | slurred speech
chest pain | swelling of the face or throat
weakness in one part or side of your body

Stop taking your NSAID and call your healthcare provider right away if you get any of the following symptoms:

nausea

vomit blood

more tired or weaker than usual

there is blood in your bowel movement or it is black and sticky like tar

diarrhea

unusual weight gain

itching

skin rash or blisters with fever

your skin or eyes look yellow

swelling of the arms, legs, hands and feet

indigestion or stomach pain

flu-like symptoms

If you take too much of your NSAID, call your healthcare provider or get medical help right away.

These are not all the possible side effects of NSAIDs. For more information, ask your healthcare provider or pharmacist about NSAIDs. Call your doctor for medical advice about side effects. You may report side effects to FDA at 1-800-FDA-1088.

Other information about NSAIDs

Aspirin is an NSAID but it does not increase the chance of a heart attack. Aspirin can cause bleeding in the brain, stomach, and intestines. Aspirin can also cause ulcers in the stomach and intestines.
Some NSAIDs are sold in lower doses without a prescription (over-the counter). Talk to your healthcare provider before using over-the-counter NSAIDs for more than 10 days.

General information about the safe and effective use of NSAIDs

Medicines are sometimes prescribed for purposes other than those listed in a Medication Guide. Do not use NSAIDs for a condition for which it was not prescribed. Do not give NSAIDs to other people, even if they have the same symptoms that you have. It may harm them.

If you would like more information about NSAIDs, talk with your healthcare provider. You can ask your pharmacist or healthcare provider for information about NSAIDs that is written for health professionals.

This Medication Guide has been approved by the U.S. Food and Drug Administration.

Distributed by:

Amneal Pharmaceuticals LLC

Bridgewater, NJ 08807

Rev. 11-2017-04